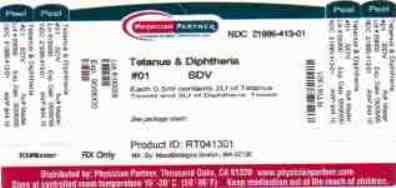 DRUG LABEL: Tetanus and Diphtheria Toxoids Adsorbed
NDC: 21695-413 | Form: INJECTION
Manufacturer: Rebel Distributors
Category: other | Type: VACCINE LABEL
Date: 20090729

ACTIVE INGREDIENTS: CLOSTRIDIUM TETANI 2.0 1/0.5 mL; CORYNEBACTERIUM DIPHTHERIAE 2.0 1/0.5 mL
INACTIVE INGREDIENTS: ALUMINUM PHOSPHATE; Formaldehyde

Tetanus and Diphtheria Toxoids Adsorbed

DESCRIPTION

Tetanus and Diphtheria Toxoids Adsorbed (Td) manufactured by MassBiologics is a sterile vaccine for intramuscular injection. After shaking, the vaccine appears as a homogenous milky white suspension.
Each 0.5 ml dose of MassBiologics' Td is formulated to contain the following active ingredients: 2 Lf of tetanus toxoid and 2 Lf of diphtheria toxoid. Each 0.5 ml dose also contains aluminum adjuvant (not more than 0.53 mg aluminum by assay), < 100 mcg (0.02%) of residual formaldehyde, and a trace amount of thimerosal [mercury derivative, (≤ 0.3 mcg mercury/dose)] (not as a preservative) from the manufacturing process. MassBiologics' Td does not contain a preservative.
The Corynebacterium diphtheriae and Clostridium tetani organisms are grown on modified Mueller's media^1,2 which contains bovine extracts. The bovine material used in these extracts is sourced from countries which the United States Department of Agriculture has determined neither have nor present an undue risk for bovine spongiform encephalopathy. Tetanus and diphtheria toxins produced during growth of the cultures are detoxified with formaldehyde. The detoxified materials are then separately purified by ammonium sulfate fractionation. The diphtheria toxoid is further purified by column chromatography. The tetanus and diphtheria toxoids are individually adsorbed onto aluminum phosphate.
The tetanus and diphtheria toxoids induce at least 2 units and 1 unit of antitoxin per ml of serum, respectively, in the guinea pig potency test.

CLINICAL PHARMACOLOGY

TETANUS
Tetanus (also known as lockjaw) is a serious, often fatal disease caused by an extremely potent neurotoxin produced by C. tetani.
Protection against disease is due to the development of neutralizing antibodies to tetanus toxin. A serum tetanus antitoxin level of 0.01 IU/ml measured via a neutralization assay is considered the minimum protective level.^3,4 The efficacy against tetanus of MassBiologics' Td is supported by the following:
1. Response to primary series. Of 20 adults with less than 0.0025 units/ml of tetanus antitoxin in pre-immunization serum, 14 (70%) had antitoxin concentrations of 0.01 or greater after 2 doses of Td (2 Lf tetanus toxoid dose). After 3 doses of Td, 16 of 16 adults achieved 0.01 antitoxin units/ml.
2. Response to booster doses. Booster doses of Td at doses of 1 Lf and 5 Lf of tetanus toxoid induced tetanus antitoxin levels greater than 0.01 units/ml when administered to all 36 adults who had received prior tetanus immunizations.^5
DIPHTHERIA
Diphtheria is an acute toxin-mediated disease caused by toxigenic strains of C. diphtheriae. Protection against disease is due to the development of neutralizing antibodies to diphtheria toxin. A serum diphtheria antitoxin level of 0.01 IU/ml is the lowest level giving some degree of protection.^(3, 6) The efficacy against diphtheria of MassBiologics' Td is supported by the following:
1. Response to primary series. Of 10 adults with less than 0.001 units/ml of diphtheria antitoxin in pre-immunization serum, 50% had antitoxin concentrations of 0.01 or greater after 2 doses of Td (2 Lf diphtheria toxoid dose). After 3 doses of Td, 6 of 6 adults achieved 0.01 antitoxin units/ml.
2. Response to booster doses. In clinical trials, booster doses of Td formulated to contain 1 Lf and 5 Lf of diphtheria toxoid, both induced antitoxin levels greater than 0.01 units/ml when administered to adults with prior diphtheria immunity.^(5, 7, 8) In 140 adolescent males given a single booster dose of the 1 Lf formulation, all achieved an antitoxin titer of 0.01 units/ml or higher.^8

INDICATIONS AND USAGE

MassBiologics' Td is a vaccine indicated for active immunization for the prevention of tetanus and diphtheria. This vaccine is approved for use in persons 7 years of age and older.

CONTRAINDICATIONS

A severe allergic reaction (e.g., anaphylaxis) occurring after a previous dose of this vaccine, or any other tetanus or diphtheria toxoid-containing vaccine, or any component of this vaccine is a contraindication to administration of MassBiologics' Td vaccine. (See DESCRIPTION). Because of the uncertainty as to which component of the vaccine might be responsible, no further vaccination with diphtheria or tetanus components should be carried out. Alternatively, such individuals may be referred to an allergist for evaluation if further immunizations are to be considered.

WARNINGS

FREQUENCY OF ADMINISTRATION

More frequent administration of MassBiologics' Td than described in DOSAGE AND ADMINISTRATION may be associated with an increased incidence and severity of adverse reactions.

ARTHUS REACTIONS

Persons who experienced an Arthus-type hypersensitivity reaction following a prior dose of a tetanus toxoid-containing vaccine usually have high serum tetanus antitoxin levels and should not receive MassBiologics' Td more frequently than every 10 years, even for tetanus prophylaxis as part of wound management. (See DOSAGE AND ADMINISTRATION).

GUILLAIN-BARRÉ SYNDROME

A review by the Institute of Medicine found evidence for a causal relation between tetanus toxoid and Guillain-Barré Syndrome.^9 If Guillain-Barré Syndrome occurred within 6 weeks after receipt of a previous dose of tetanus toxoid-containing vaccine, the decision to give subsequent doses of MassBiologics' Td or any vaccine containing tetanus toxoid should be based on careful consideration of the potential benefits and possible risks.^10

Vaccination with MassBiologics' Td may not protect all individuals.

PRECAUTIONS

GENERAL

Epinepherine injection (1:1000) and other appropriate agents and equipment must be immediately available should an acute anaphylactic reaction occur.

Prior to the administration of MassBiologics' Td, the vaccine recipient's current health status and health history should be reviewed. This includes a review of the immunization history of the patient, the presence of any contraindications to immunization, and any adverse events after previous immunizations to allow an assessment of the benefits and risks of vaccination. (See CONTRAINDICATIONS and WARNINGS).

If MassBiologics' Td is administered to immunocompromised persons (whether from disease or treatment) the expected immune response may not be obtained.

INFORMATION FOR PATIENTS

Prior to administration of MassBiologics' Td, patients, parents or guardians should be informed by the health care provider of the benefits and risks of immunization with Td and of the importance of completing the primary immunization series or receiving recommended booster doses.

The health care provider should inform the patient, parent, or guardian of the potential for adverse reactions that have been temporally associated with MassBiologics' Td or other vaccines containing similar ingredients. Patients, parents or guardians should be instructed to report any suspected adverse reactions to their health care provider.

According to the National Childhood Vaccine Injury Act of 1986, Vaccine Information Statements must be provided by the health care provider with each vaccine dose administered.

DRUG INTERACTIONS

Patients who are on immunosuppressive therapy, including alkylating agents, antimetabolites, cytotoxic drugs, irradiation, or corticosteroids (used in greater than physiologic doses), may have a reduced immune response to vaccines.

No safety and immunogenicity data are available on the concomitant administration of MassBiologics' Td vaccine with other U.S. licensed vaccines.

CARCINOGENESIS, MUTAGENESIS, IMPAIRMENT OF FERTILITY

No studies have been performed with MassBiologics' Td to evaluate carcinogenicity, mutagenic potential or impairment of fertility.

PREGNANCY CATEGORY C

Animal reproduction studies have not been conducted with MassBiologics' Td. It is also not known whether MassBiologics' Td can cause fetal harm when administered to a pregnant woman or can affect reproduction capacity. MassBiologics' Td should be given to a pregnant woman only if clearly needed.

NURSING MOTHERS

It is not known whether MassBiologics' Td is excreted in human milk. Because many drugs are excreted in human milk, caution should be exercised when MassBiologics' Td is administered to a nursing woman.

PEDIATRIC USE

MassBiologics' Td is not approved for use in infants and children younger then 7 years of age. The safety and effectiveness of MassBiologics' Td in this age group have not been established.

GERIATRIC USE

No studies have been performed with MassBiologics' Td in adults aged 65 years and older in order to determine whether they respond differently than younger subjects.

ADVERSE REACTIONS

DATA FROM CLINICAL TRIALS
Because clinical trials are conducted under widely varying conditions, adverse reaction rates observed in the clinical trials of a vaccine cannot be directly compared to rates in the clinical trials of another vaccine, and may not reflect the rates observed in practice. However, the adverse reaction information from clinical trials provides a basis for identifying adverse events that appear to be related to vaccine use and for approximating rates. Data on adverse reactions following fluid and adsorbed preparations of MassBiologics' Td with various doses of the diphtheria and tetanus components have been reported in a series of studies.^(5, 7, 8, 11, 12)
POSTMARKETING REPORTS
The following adverse events have been identified during post-approval use of MassBiologics' Td. Because these reactions are reported voluntarily from a population of uncertain size, it is not always possible to reliably estimate their frequencies or to establish a causal relationship to vaccination. The following adverse events were included because of seriousness or frequency of reporting:
General Disorders and Administration Site Conditions: Injection site reactions, including pain, tenderness, erythema, induration, pruritis, swelling and warmth; peripheral oedema, pyrexia, malaise
Nervous System Disorders: Dizziness, headache, convulsions
Musculoskeletal and Connective Tissue Disorders: Myalgia, musculoskeletal stiffness or pain, arthralgia
Skin and Subcutaneous Tissue Disorders: Rash
Gastrointestinal Disorders: Nausea
Infections and Infestations: Cellulitis
REPORTING OF SUSPECTED ADVERSE REACTIONS
To report SUSPECTED ADVERSE REACTIONS, contact MassBiologics at 1-800-457-4626 or VAERS at 1-800-822-7967 or www.vaers.hhs.gov.

DOSAGE AND ADMINISTRATION

PRIMARY IMMUNIZATION

MassBiologics' Td may be used in persons 7 years of age and older who have not been previously immunized against tetanus and diphtheria, as a primary immunization series consisting of three 0.5 ml doses. The first two doses are administered 4-8 weeks apart and the third dose is administered 6-12 months after the second dose.

MassBiologics' Td may be used to complete the primary immunization series for tetanus and diphtheria, following one or two doses of Diphtheria and Tetanus Toxoids and Pertussis Vaccine Adsorbed (whole-cell DTP), Diphtheria and Tetanus Toxoids and Acellular Pertussis Vaccine Adsorbed (DTaP) and/or Diphtheria and Tetanus Toxoids Adsorbed (DT) vaccine. However, the safety and efficacy of MassBiologics' Td in such regimens have not been evaluated.

ROUTINE BOOSTER IMMUNIZATION

MassBiologics' Td may be used for routine booster immunization against tetanus and diphtheria in persons 7 years of age and older who have completed primary immunization against tetanus and diphtheria. Routine booster immunization against tetanus and dipthheria is recommended in children 11-12 years of age and every 10 years thereafter.^10

The Advisory Committee on Immunization Practices (ACIP) has specific recommendations on booster immunization against tetanus and diphtheria for adolescents and adults.^(10, 13, 14)

TETANUS PROPHYLAXIS IN WOUND MANAGEMENT

For active tetanus immunization in wound management of patients 7 years of age and older, a preparation containing tetanus and diphtheria toxoids is preferred instead of single-antigen tetanus toxoid to enhance diphtheria protection.^15 MassBiologics' Td is approved for wound management of patient 7 years of age and older.

The need for active immunization with a tetanus toxoid-containing preparation, with or without Tetanus Immune Globulin (TIG) (Human) depends on both the condition of the wound and the patient's vaccination history (Table 1).

When indicated, TIG (Human) should be administered using a separate needle and syringe at a different anatomic site, according to the manufacturer's package insert. If a contraindication to using a tetanus toxoid-containing vaccine exists in a person who has not completed tetanus primary immunization and other than a clean, minor wound is sustained, only passive immunization with TIG (Human) should be given.^15

TABLE 1 GUIDE TO TETANUS PROPHYLAXIS IN ROUTINE WOUND MANAGEMENT IN PERSONS AGED 7 YEARS AND OLDER^(13, 14, 15)

History of Adsorbed Tetanus Toxoid (Doses) | Clean, Minor Wounds |  | All Other Wounds*
History of Adsorbed Tetanus Toxoid (Doses) |  | Td† | TIG | Td † | TIG
Unknown or < 3 | Yes | No | Yes | Yes
> 3‡ | No§ | No | No¶ | No

* Such as, but not limited to, wounds contaminated with dirt, feces, soil, and saliva; puncture wounds; avulsions; and wounds resulting from missiles, crushing, burns and frostbite.
† The ACIP has specific recommendations on use of Td or Tetanus Toxoid, Reduced Diphtheria Toxoids and Acellular Pertussis Vaccine Adsorbed (Tdap) in adolescents and adults.^13,14
‡ If only three doses of fluid tetanus toxoid have been received, then a fourth dose of toxoid, preferably an adsorbed toxoid, should be given.
§ Yes, if > 10 years since the last tetanus toxoid-containing vaccine dose.
¶ Yes, if > 5 years since the last tetanus toxoid-containing vaccine dose. (More frequent boosters are not needed and can accentuate side effects.)
DIPHTHERIA PROPHYLAXIS FOR CASE CONTACTS
MassBiologics' Td may be used for post-exposure diphtheria prophylaxis in persons 7 years of age and older who have not completed primary vaccination, whose vaccination status is unknown, or who have not been vaccinated with diphtheria toxoid within the previous 5 years. Consult ACIP recommendations for additional interventions for post-exposure diphtheria prophylaxis.^15
ADMINISTRATION
Shake the vial well to resuspend the vaccine before withdrawing the dose. After shaking, MassBiologics' Td is a homogenous milky white suspension. Parenteral drug products should be inspected visually for particulate matter and discoloration prior to administration, whenever solution and container permit. If these conditions exist, MassBiologics' Td should not be administered.
Inject 0.5 ml of MassBiologics' Td intramuscularly. The preferred site is the deltoid muscle. The vaccine should not be injected into the gluteal area or areas where there may be a major nerve trunk.
Do not administer this vaccine intravenously, subcutaneously, or intradermally.
MassBiologics' Td should not be combined through reconstitution or mixed with any other vaccine.

HOW SUPPLIED

The stopper of the vial is latex free.
MassBiologics' Td is supplied in single-dose (0.5 ml) vials.
NDC No. 14362-0111-3 - Package of 10 single dose vials.

STORAGE

Store at 2oC - 8oC (36oF - 46oF). DO NOT FREEZE. Discard product if exposed to freezing.

Do not use vaccine after expiration date.

REFERENCES

1. Latham WC, Bent DF, and Levine L. Tetanus toxin production in the absence of protein. Appl. Microbiol. 10(2): March 1962;146-152.
2. Mueller JH and Miller PA. Production of diphtheric toxin of high potency (100 Lf) on a reproducible medium. J. Immunol. 40: 1941;21-32.
3. Food and Drug Administration. Department of Health and Human Services (DHHS). Biological Products; bacterial vaccines and toxoids; implementation of efficacy review; proposed rule. Fed Reg 1985;50(240): 51002-117.
4. Wassilak SGF, et al. Tetanus toxoid. In: Plotkin SA, Orenstein WA, Offit PA, editors. Vaccines. 5th ed. Philadelphia, PA: WB Saunders Company; 2008. p. 805-839.
5. Ipsen J. Jr. Immunization of adults against diphtheria and tetanus. NEJM. 1954; 251:459-466.
6. Vitek CR and Wharton M. Diphtheria toxoid. In: Plotkin SA, Orenstein WA, Offit PA, editors. Vaccines. 5th ed. Philadelphia, PA: WB Saunders Company; 2008. p. 139-156.
7. Edsall G, Altman JS, and Gaspar AJ. Combined tetanus-diphtheria immunization of adults: Use of small doses of diphtheria toxoid. Am J Public Health Nations Health. 1954 Dec;44(12):1537-1545.
8. Levine L, Ipsen J, and McComb JA. Adult immunization: preparation and evaluation of combined fluid tetanus and diphtheria toxoids for adult use. AM. J. Hyg. 1961;73:20-35.
9. Institute of Medicine. Stratton KR, et al, eds. Adverse Events Associated with Childhood Vaccines: Evidence Bearing on Casuality. Washington D.C.: National Academy Press. 1994:67-117.
10. Centers for Disease Control and Prevention. General recommendations on immunization: recommendations of the Advisory Committee on Immunization Practices (ACIP). MMWR 2006;55(No. RR-15):1-48.
11. McComb JA and Levine L. Adult immunization II. Dosage reduction as a solution in increasing reactions to tetanus toxoid. NEJM. 1961;256:1152-1158.
12. Levine L and Edsall G. Tetanus toxoid: What determines reaction proneness? J. Infect. Dis. 1981;144:376.
13. Centers for Disease Control and Prevention. Preventing tetanus, diphtheria, and pertussis among adolescents: use of tetanus toxoid, reduced diphtheria toxoid and acellular pertussis vaccines: recommendations of the Advisory Committee on Immunization Practices (ACIP). MMWR 2006;55(No. RR-3):1-43.
14. Centers for Disease Control and Prevention. Preventing tetanus, diphtheria, and pertussis among adults: use of tetanus toxoid, reduced diphtheria toxoid and acellular pertussis vaccine. Recommendations of the Advisory Committee on Immunization Practices (ACIP) and recommendations of ACIP, supported by the Healthcare Infection Control Practices Advisory Committee (HICPAC), for use of Tdap among health-care personnel. MMWR 2006;55(No. RR-17):1-37.
15. Centers for Disease Control and Prevention. Recommendations of the Immunization Practices Advisory Committee (ACIP). Diphtheria, tetanus, and pertussis: recommendations for vaccine use and other preventative measures. MMWR 1991;40(No. RR-10):1-35.
Manufactured by:
MassBiologics
University of Massachusetts Medical School
Boston, MA 02130
US Government License No. 1779
Repackaged by:
Rebel Distributors Corp.
Thousand Oaks, CA 91320